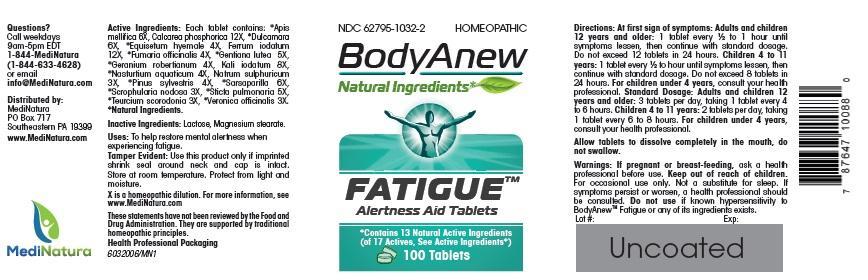 DRUG LABEL: BodyAnew Fatigue HCP
NDC: 62795-1032 | Form: TABLET
Manufacturer: MediNatura Inc
Category: homeopathic | Type: HUMAN OTC DRUG LABEL
Date: 20150309

ACTIVE INGREDIENTS: APIS MELLIFERA 6 [hp_X]/1 1; TRIBASIC CALCIUM PHOSPHATE 12 [hp_X]/1 1; SOLANUM DULCAMARA TOP 6 [hp_X]/1 1; EQUISETUM HYEMALE 4 [hp_X]/1 1; FERROUS IODIDE 12 [hp_X]/1 1; FUMARIA OFFICINALIS FLOWERING TOP 4 [hp_X]/1 1; GENTIANA LUTEA ROOT 5 [hp_X]/1 1; GERANIUM ROBERTIANUM 4 [hp_X]/1 1; POTASSIUM IODIDE 8 [hp_X]/1 1; NASTURTIUM OFFICINALE 4 [hp_X]/1 1; SODIUM SULFATE 3 [hp_X]/1 1; PINUS SYLVESTRIS LEAFY TWIG 4 [hp_X]/1 1; SMILAX REGELII ROOT 6  [hp_X]/1 1; SCROPHULARIA NODOSA 3 [hp_X]/1 1; LOBARIA PULMONARIA 5 [hp_X]/1 1; TEUCRIUM SCORODONIA FLOWERING TOP 3 [hp_X]/1 1
INACTIVE INGREDIENTS: LACTOSE; MAGNESIUM STEARATE

BodyAnew Fatigue HCP Tablet

USES

To help restore mental alertness when experiencing fatigue.

ACTIVE INGREDIENT

*Apis mellifica 6X, Calcarea phosphorica 12X, *Dulcamara 6X, *Equisetum hyemale 4X, Ferrum iodatum 12X, *Fumaria officinalis 4X, *Gentiana lutea 5X, *Geranium robertianum 4X, Kali iodatum 8X, *Nasturtium aquaticum 4X, Natrum sulphuricum 3X, *Pinus sylvestris 4X, *Sarsaparilla 6X,*Scrophularia nodosa 3X, *Sticta pulmonaria 5X, *Teurcium scorodonia 3X, *Veronica officinalis 3X.

*Natural Ingredients.

INACTIVE INGREDIENT

Lactose, Magnesium stearate.

PURPOSE

Alertness Aid

Directions

At first sign of symptoms: Adults and children 12 years and older: 1 tablet every ½ to 1 hour until symptoms lessen, then continue with standard dosage. Do not exceed 12 tablets in 24 hours. Children 4 to 11 years: 1 tablet every ½ to hour until symptoms lessen, then continue with standard dosage. Do not exceed 8 tablets in 24 hours.

For children under 4 years, consult your health professional.

Standard Dosage: Adults and children 12 years and older: 3 tablets per day, taking 1 tablet every 4 to 6 hours.

Children 4 to 11 years: 2 tablets per day, taking 1 tablet every 6 to 8 hours.

For children under 4 years, consult your health professional.

Allow tablets to dissolve completely in the mouth, do not swallow.

WARNINGS

If pregnant or breast-feeding, ask a health professional before use.

Keep out of reach of children. For occasional use only. Not a substitute for sleep. If symptoms persist or worsen, a health professional should be consulted. Do not use if known hypersensitivity to BodyAnewTM Fatigue or any of its ingredients exists.

KEEP OUT OF REACH OF CHILDREN